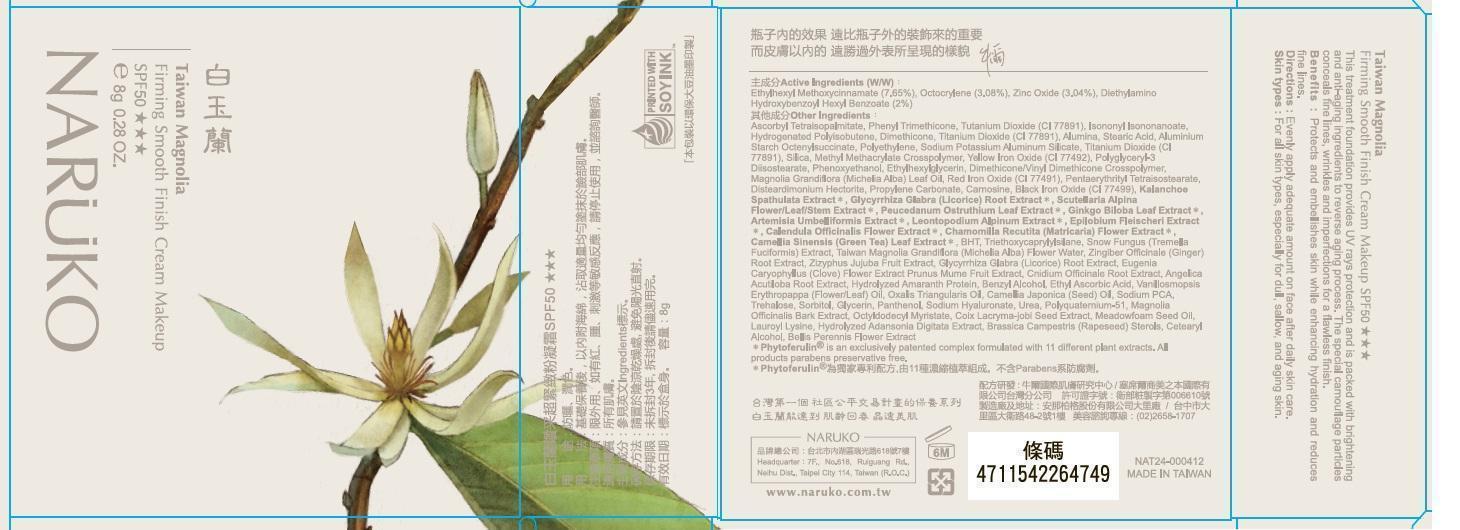 DRUG LABEL: Naruko
NDC: 69003-412 | Form: CREAM
Manufacturer: Beauty Essentials Limited, Taiwan Branch
Category: otc | Type: HUMAN OTC DRUG LABEL
Date: 20140508

ACTIVE INGREDIENTS: OCTINOXATE 7.65 g/100 g; OCTOCRYLENE 3.08 g/100 g; ZINC OXIDE 3.04 g/100 g
INACTIVE INGREDIENTS: DIETHYLAMINO HYDROXYBENZOYL HEXYL BENZOATE; ASCORBYL TETRAISOPALMITATE; PHENYL TRIMETHICONE; TITANIUM DIOXIDE; ISONONYL ISONONANOATE; HYDROGENATED POLYBUTENE (1300 MW); DIMETHICONE; ALUMINUM OXIDE; STEARIC ACID; ALUMINUM STARCH OCTENYLSUCCINATE; HIGH DENSITY POLYETHYLENE; SODIUM SILICATE; POTASSIUM SILICATE; ALUMINUM SILICATE; SILICON DIOXIDE; METHYL METHACRYLATE/GLYCOL DIMETHACRYLATE CROSSPOLYMER; FERRIC OXIDE YELLOW; POLYGLYCERYL-3 DIISOSTEARATE; PHENOXYETHANOL; ETHYLHEXYLGLYCERIN; DIMETHICONE/VINYL DIMETHICONE CROSSPOLYMER (SOFT PARTICLE) ; MAGNOLIA GRANDIFLORA LEAF; FERRIC OXIDE RED; PENTAERYTHRITYL TETRAISOSTEARATE; DISTEARDIMONIUM HECTORITE; PROPYLENE CARBONATE; CARNOSINE; FERROSOFERRIC OXIDE; KALANCHOE PINNATA LEAF; GLYCYRRHIZA GLABRA; SCUTELLARIA ALPINA FLOWERING TOP; PEUCEDANUM OSTRUTHIUM LEAF; GINKGO; ARTEMISIA UMBELLIFORMIS WHOLE; LEONTOPODIUM ALPINUM; EPILOBIUM ANGUSTIFOLIUM WHOLE; CALENDULA OFFICINALIS FLOWER; CHAMOMILE; GREEN TEA LEAF; BUTYLATED HYDROXYTOLUENE; TRIETHOXYCAPRYLYLSILANE; TREMELLA FUCIFORMIS WHOLE; MAGNOLIA X ALBA FLOWER OIL; GINGER; JUJUBE FRUIT; CLOVE; PRUNUS MUME FRUIT; CNIDIUM OFFICINALE ROOT; ANGELICA ACUTILOBA ROOT; AMARANTHUS HYPOCHONDRIACUS WHOLE; BENZYL ALCOHOL; 3-O-ETHYL ASCORBIC ACID; TAGETES ERECTA WHOLE; OXALIS CORNICULATA WHOLE; CAMELLIA JAPONICA SEED OIL; SODIUM PYRROLIDONE CARBOXYLATE; TREHALOSE; SORBITOL; GLYCERIN; PANTHENOL; HYALURONATE SODIUM; UREA; POLYQUATERNIUM-51 (2-METHACRYLOYLOXYETHYL PHOSPHORYLCHOLINE/N-BUTYL METHACRYLATE; 3:7); MAGNOLIA OFFICINALIS BARK; OCTYLDODECYL MYRISTATE; COIX LACRYMA-JOBI SEED; MEADOWFOAM SEED OIL; LAUROYL LYSINE; ADANSONIA DIGITATA WHOLE; RAPESEED STEROL; CETOSTEARYL ALCOHOL; BELLIS PERENNIS FLOWER

NARUKO

Active ingredients

Ethylhexyl Methoxycinnamate (7.65%), Octocrylene(3.08%), Zinc Oxide(3.04%)

Purpose

Sunscreen

Keep out of reach of children. If product is swallowed, get medical help or contact a Poison Control Center right away.

Uses

helps prevent sunburn

Warnings

For external use only

Do not use on damaged or broken skin

When using this product keep out of eyes. Rinse with water to remove.

Stop use and ask a doctor if rash occurs.

Directions

apply liberally 15 minutes before sun exposure.

Inactive ingredients

Diethylamino hydroxybenzoyl hexyl benzoate, Ascorbyl tetraisopalmitate, Phenyl trimethicone, Titanium dioxide,Isononyl isononanoate,Hydrogenated Polyisobutene, Dimethicone, Alumina, Stearic acid, Aluminum starch octenylsuccinate, Polyethylene, Sodium Potassium Aluminum Silicate, Silica, Methyl Methacrylate Crosspolymer, Yellow Iron Oxide, Polyglyceryl-3 Diisostearate, Phenoxyethanol, Ethylhexylglycerin, Dimethicone/Vinyl dimethicone crosspolymer, Magnolia Grandiflora(Michelia Alba) Leaf oil, Red Iron Oxide, Pentaerythrityl Tetraisostearate, Disteardimonium Hectorite, Propylene carbonate, Carnosine, Black Iron oxide, Kalanchoe Spathulata Extract, Glycyrrhiza Glabra (Licorice) root extract, Scutellaria Alpina Flower/Leaf/ Stem Extract, Peucedanam Ostruthium Leaf Extract, Ginkgo Biloba Leaf Extract, Artemisia Umbelliformis Extract, Leontopodium Alpinum Extract, Epilobium Fleischeri Extract, Calendula Officinalis Flower Extract, Chamomilla Recutita (Matricaria) Flower Extract, Camellia Sinensis (Green Tea) Leaf Extract, BHT, Triethoxycaprylylsilane, Snow Fungus (Tremella Fuciformis extract), Taiwan Magnolia Grandiflora (Michelia Alba) Flower Water, Zingiber Officinale (Ginger) Root Extract, Zizyphus Jujuba Fruit Extract, Eugenia Caryophillus(Clove) flower extract, Prunus Mume Fruit Extract, Cnidium Officinale root Extract, Angelica Acutiloba Root Extract, Hydrolysed Amaranth Protein, Benzyl Alcohol, Ethyl Ascorbic Acid, Vanillomopsis Erythropappa (Flower/Leaf) Oil, Oxalis Triangularis Oil, Camellia Japonica seed oil, Sodium PCA, Trehalose, Sorbitol, Glycerin, Panthenol, Sodium Hyaluronate, Urea, Polyquaternium-51, Magnolia Officinalis bark Extract, Octyldodecyle Myristate, Coix Lachryma- jobi seed extract, Meadowfoam Seed oil, Lauroyl Lysine, Hydrolyzed Adansonia Digitata Extract, Brassica Campestris (Rapeseed) sterols, Citearyl alcohol , Bellis Perennis Flower Extract

Questions or Comments

+886-2-2658-1707